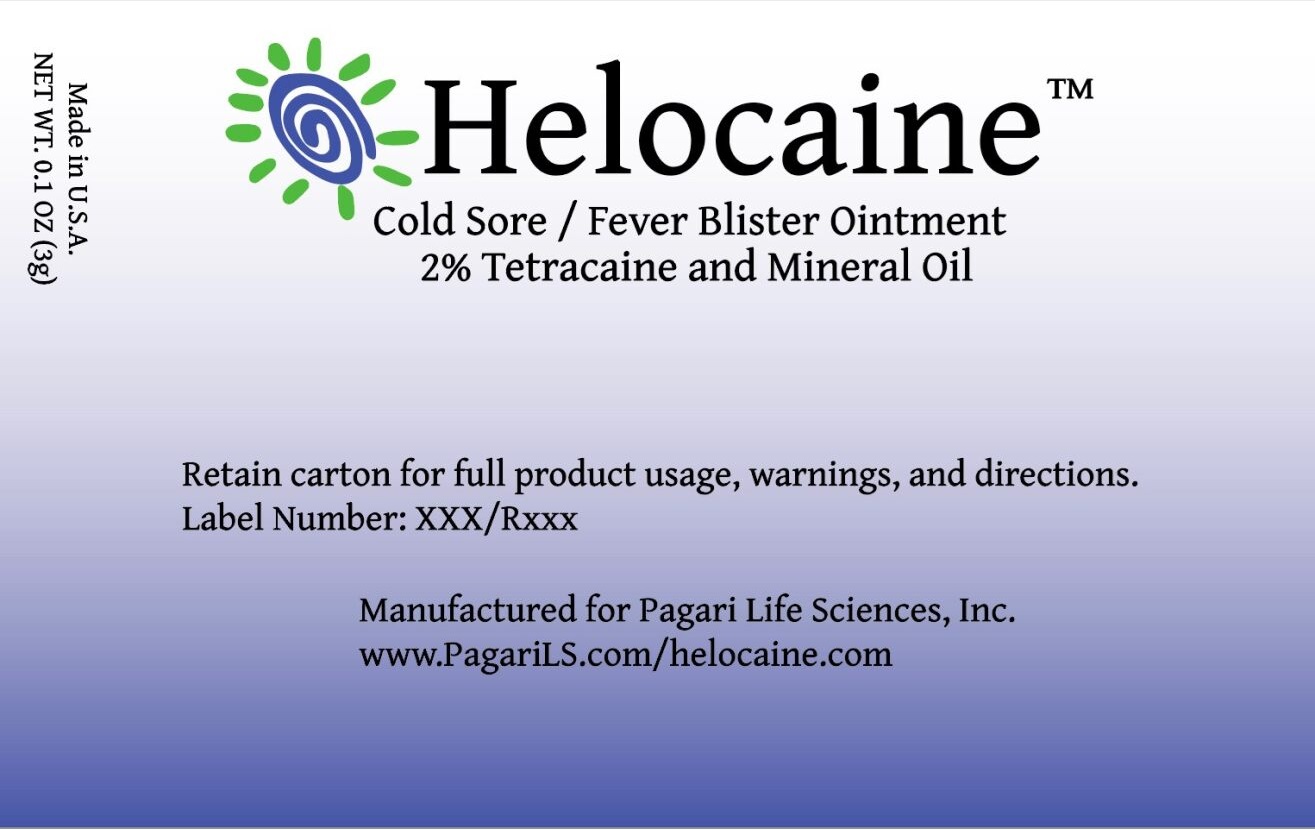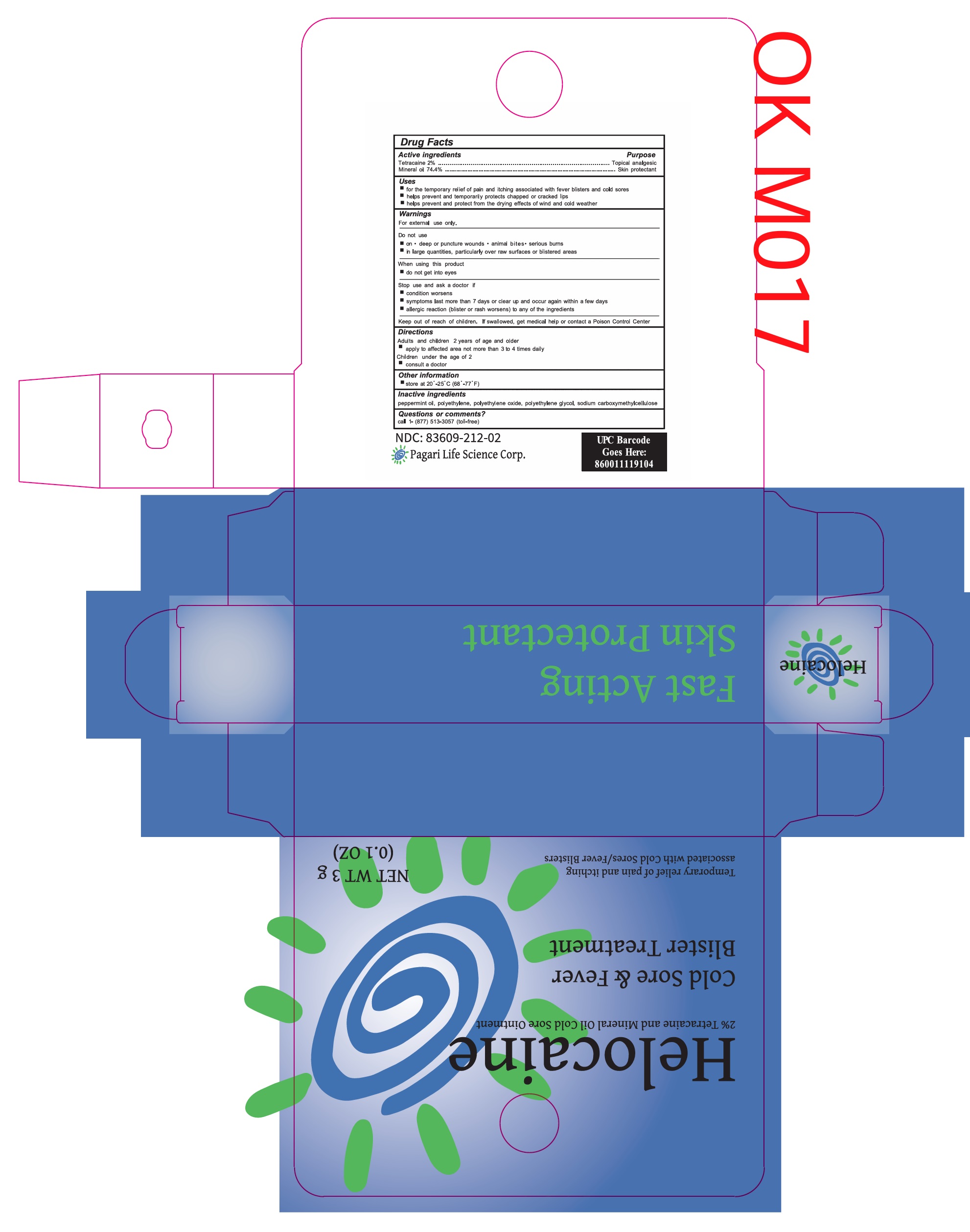 DRUG LABEL: Helocaine Cold Sore Fever Blister Treatment
NDC: 83609-212 | Form: OINTMENT
Manufacturer: Pagari Life Science Corp.
Category: otc | Type: HUMAN OTC DRUG LABEL
Date: 20260115

ACTIVE INGREDIENTS: TETRACAINE 20 mg/1 g; MINERAL OIL 744 mg/1 g
INACTIVE INGREDIENTS: HIGH DENSITY POLYETHYLENE; CARBOXYMETHYLCELLULOSE SODIUM, UNSPECIFIED FORM; POLYETHYLENE GLYCOL, UNSPECIFIED; PEPPERMINT OIL

Helocaine Cold Sore Fever Blister Treatment

Active ingredients

Tetracaine 2%

Mineral oil 74.4%

Purpose

Topical analgesic

Skin protectant

Uses

- for the temporary relief of pain and itching associated with fever blisters and cold sores
- helps prevent and temporarily protects chapped or cracked lips
- helps prevent and protect from the drying effects of wind and cold weather

Warnings

For external use only.

Do not use

- on • deep or puncture wounds • animal bites • serious burns
- in large quantities, particularly over raw surfaces or blistered areas

When using this product

- do not get into eyes

Stop use and ask a doctor if

- condition worsens
- symptoms last more than 7 days or clear up and occur again within a few days
- allergic reaction (blister or rash worsens) to any of the ingredients

Keep out of reach of children.

If swallowed, get medical help or contact a Poison Control Center

Directions

Adults and children 2 years of age and older

- apply to affected area not more than 3 to 4 times daily

Children under the age of 2

- consult a doctor

Other information

- store at 20º - 25º C (68º - 77º F)

Inactive ingredients

peppermint oil, polyethylene, polyethylene oxide, polyethylene glycol, sodium carboxymethylcellulose

Questions or comments?

call 1- (877) 513-3057 (toll-free)